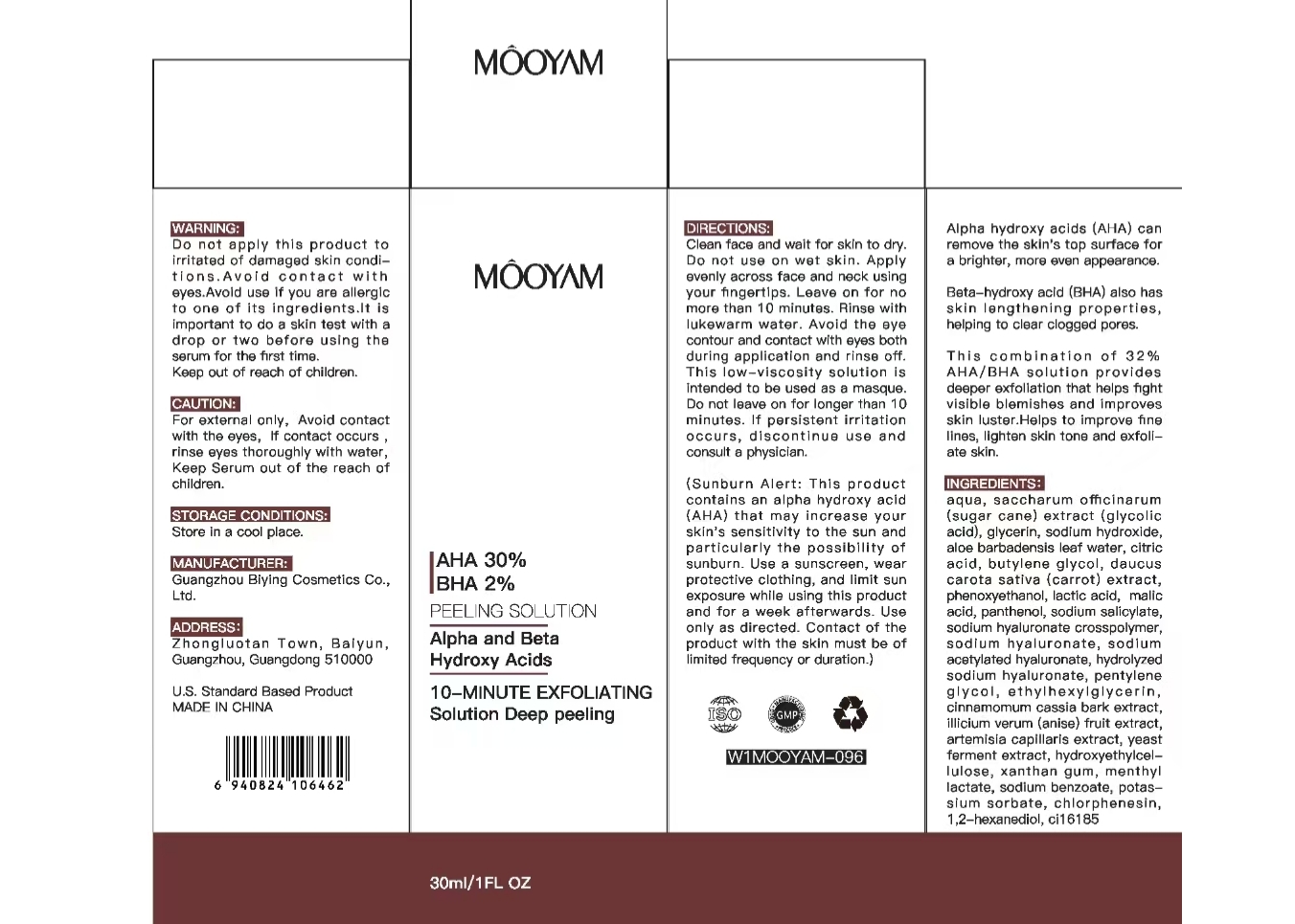 DRUG LABEL: MOOYAM AHA BHA FACE SERUM
NDC: 84507-025 | Form: LIQUID
Manufacturer: Guangdong Miaolian Cosmetics Co., Ltd.
Category: otc | Type: HUMAN OTC DRUG LABEL
Date: 20241224

ACTIVE INGREDIENTS: MALIC ACID 0.0005 mg/100 mL
INACTIVE INGREDIENTS: GLYCERIN; XANTHAN GUM; CI 19140; PENTYLENE GLYCOL; SODIUM ACETYLATED HYALURONATE; PEG-9 DIGLYCIDYL ETHER/SODIUM HYALURONATE CROSSPOLYMER; SODIUM LAURETH SULFATE; ETHYLHEXYLGLYCERIN; SODIUM BENZOATE; POTASSIUM SORBATE; SODIUM HYDROXIDE; 1,2-HEXANEDIOL; CINNAMOMUM CASSIA BARK; PEG-50 HYDROGENATED CASTOR OIL; PANTHENOL; BUTYLENE GLYCOL; YEAST; CI 15985; PROPYLENE GLYCOL; CI 77266; CAPRYLYL GLYCOL; PHENOXYETHANOL; CHLORPHENESIN; SODIUM HYALURONATE; DAUCUS CAROTA SATIVA (CARROT) SEED OIL; ILLICIUM VERUM WHOLE; SUGARCANE; MENTHOL; NONOXYNOL-12; ARTEMISIA CAPILLARIS WHOLE; LACTIC ACID; AQUA; SODIUM SALICYLATE; SODIUM CHLORIDE; SODIUM CARBONATE; MENTHYL LACTATE; PEG-35 CASTOR OIL; ALOE BARBADENSIS LEAF WATER; HYDROXYETHYLCELLULOSE

DOSAGE AND ADMINISTRATION

- Squeeze 1-2 pumps on to fingertlps.

Apply a thin layer to clean,dry skin in the morning. Avoid eye area.

- At first, use every other day. Then up to twice a day as tolerated.

WARNINGS

1. For external use only
2. Keep away from eyes, lips, and other mucous membranes. If contact occurs,flush thoroughly with water.

INACTIVE INGREDIENT

AQUA
GLYCERIN
SACCHARUM OFFICINARUM (SUGAR CANE) EXTRACT
SODIUM HYDROXIDE
SODIUM CARBONATE
SODIUM SALICYLATE
CI 19140
SODIUM CHLORIDE
CI 15985
HYDROXYETHYLCELLULOSE
XANTHAN GUM
PHENOXYETHANOL
1,2-HEXANEDIOL
CHLORPHENESIN
PEG-50 HYDROGENATED CASTOR OIL
MENTHOL
NONOXYNOL-12
PROPYLENE GLYCOL
MENTHYL LACTATE
PEG-35 CASTOR OIL
PENTYLENE GLYCOL
SODIUM HYALURONATE
SODIUM ACETYLATED HYALURONATE
SODIUM HYALURONATE CROSSPOLYMER
HYDROLYZED SODIUM HYALURONATE
ETHYLHEXYLGLYCERIN
ALOE BARBADENSIS LEAF WATER
LACTIC ACID
PANTHENOL
BUTYLENE GLYCOL
DAUCUS CAROTA SATIVA (CARROT) EXTRACT
CINNAMOMUM CASSIA BARK EXTRACT
ILLICIUM VERUM (ANISE) FRUIT EXTRACT
ARTEMISIA CAPILLARIS EXTRACT
YEAST FERMENT EXTRACT
SODIUM BENZOATE
POTASSIUM SORBATE
CI 77266
SODIUM LAURETH SULFATE
CAPRYLYL GLYCOL

INDICATIONS AND USAGE

Gently dissolves cuticles to clear blockages and control oil secretion.

KEEP OUT OF REACH OF CHILDREN

Keep out of the reach of children. If swallowed get medical help or contact Poison Control Center right away.

PURPOSE

Skin Care.

Acne Treatment.

ACTIVE INGREDIENT

MALIC ACID -----0.005%